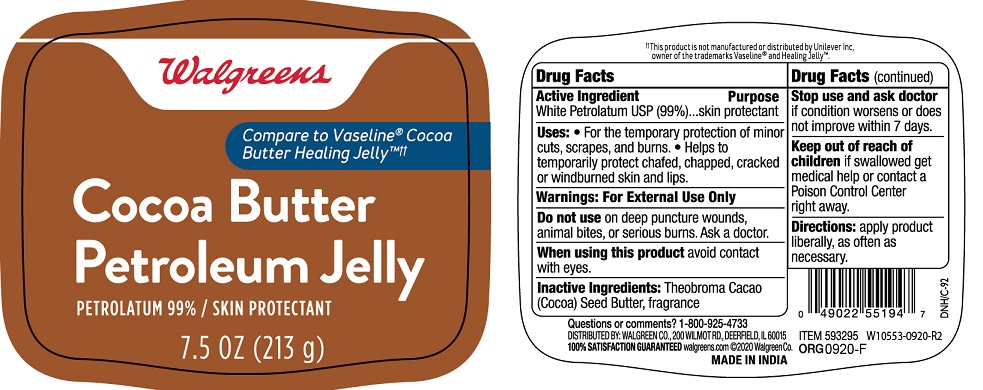 DRUG LABEL: Walgreens Cocoa Butter Jelly
NDC: 0363-0712 | Form: JELLY
Manufacturer: Walgreens
Category: otc | Type: HUMAN OTC DRUG LABEL
Date: 20260114

ACTIVE INGREDIENTS: PETROLATUM 99 g/100 g
INACTIVE INGREDIENTS: COCOA BUTTER

Walgreens®Cocoa Butter Petroleum Jelly

Active Ingredient

White Petrolatum USP (99%)

Purpose

Skin protectant

Uses

• For the temporary protection of minor cuts, scrapes, burns
• Helps to temporarily protect chafed, chapped, cracked or windburned skin and lips.

Warnings

For External Use Only

DO NOT USE

Do not useon deep puncture wounds, animal bites, or serious burns. Ask a doctor.

When using this productavoid contact with eyes.

Stop use and ask doctorif condition worsens or does not improve within 7 days.

KEEP OUT OF REACH OF CHILDREN

Keep out of reach of childrenif swallowed get medical help or contact a Poison Control Center right away.

Directions

apply product liberally, as often as necessary.

Inactive ingredients

Theobroma Cacao (Cocoa) Seed Butter, fragrance

PACKAGE LABEL

PRINCIPAL DISPLAY PANEL

COCOA BUTTER PETROLEUM JELLY

NET WT 7.5 OZ (213 g)